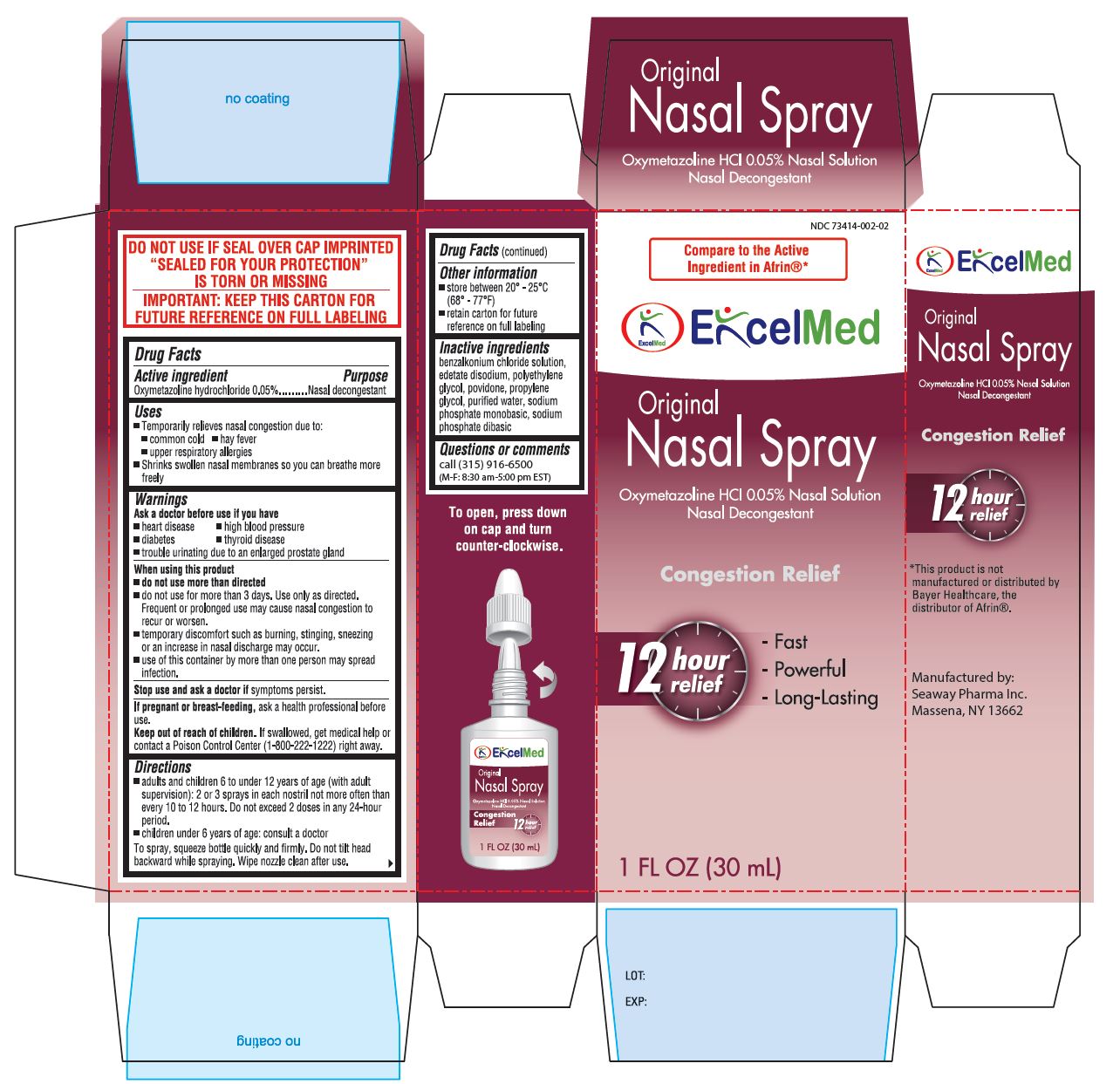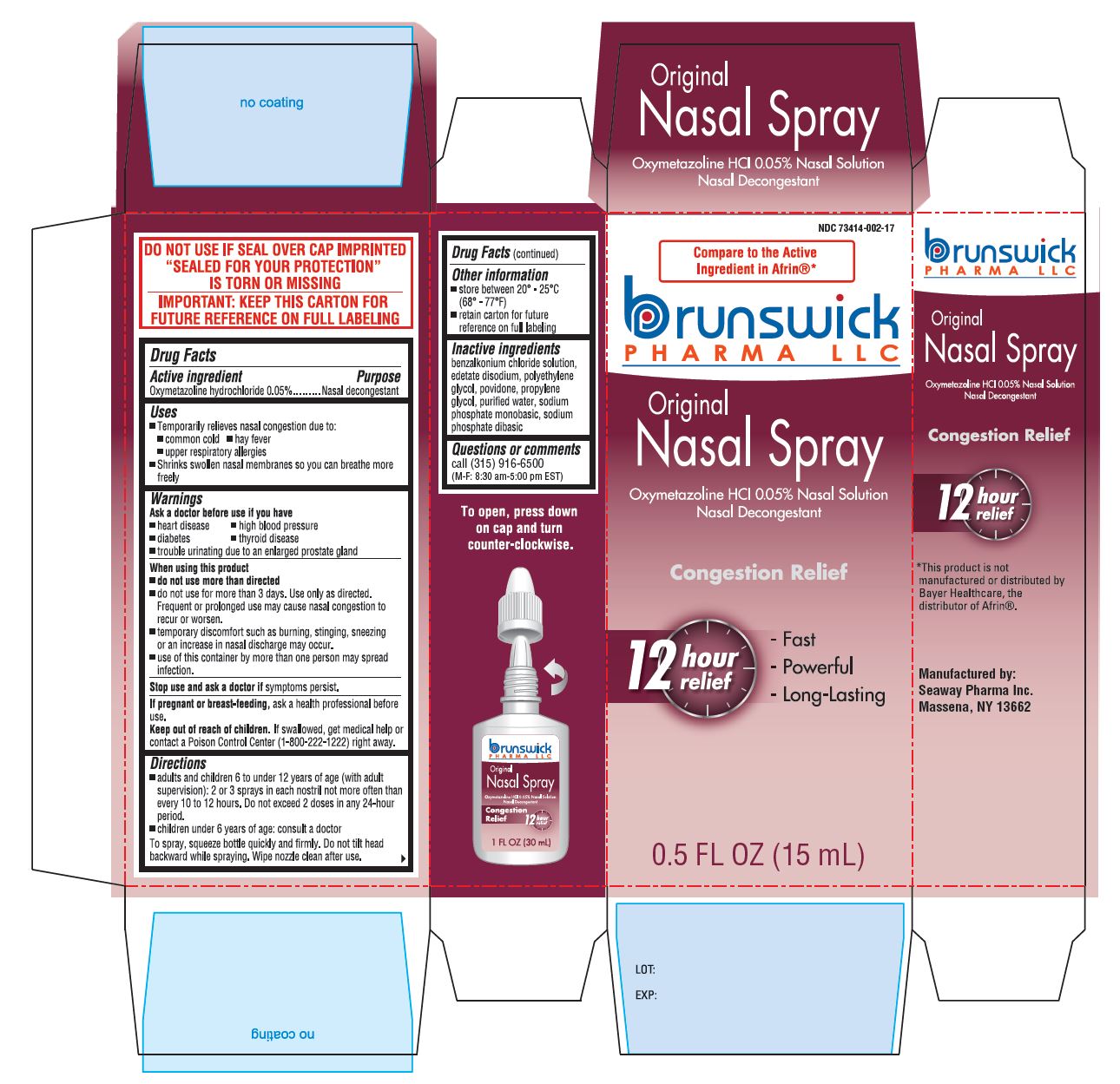 DRUG LABEL: OXYMETAZOLINE HCl
NDC: 73414-002 | Form: SPRAY
Manufacturer: Seaway Pharma Inc.
Category: otc | Type: HUMAN OTC DRUG LABEL
Date: 20200618

ACTIVE INGREDIENTS: OXYMETAZOLINE HYDROCHLORIDE 0.5 mg/1 mL
INACTIVE INGREDIENTS: BENZALKONIUM CHLORIDE; EDETATE DISODIUM; POLYETHYLENE GLYCOL, UNSPECIFIED; POVIDONE, UNSPECIFIED; PROPYLENE GLYCOL; WATER; SODIUM PHOSPHATE, MONOBASIC; SODIUM PHOSPHATE, DIBASIC

NASAL SPRAY ORIGINAL 15mL and 30mL

Active Ingredient: Oxymetazoline HCl 0.05%

Purpose: Nasal Decongestant

Uses
Temporarily relieves nasal congestion due to:

- common cold
- hay fever
- upper respiratory allergies
- shrinks swollen nasal membrances so you can breathe more freely.

WARNINGS

Ask a doctor before use if you have

- heart disease
- high blood pressure
- thyroid disease
- diabetes
- trouble urinating due to an enlarged prostate gland

When using this product:

- do not use more than directed
- do not use for more than 3 days. Use only as directed.

WHEN USING

- Frequent or prolonged use may cause nasal congestion to recur or worsen
- temporary discomfort such as burning, stinging, sneezing or an increase in nasal discharge may occur
- use of this container by more than one person may spread infection

Stop use and ask a doctor If symptoms persist.

If pregnant or breast feeding, ask a health professional before use.

Keep out of reach of children. If swallowed, get medical help or contact a Poison Control Center (1-800-222-1222) right away.

Directions

- adults and children 6 to under 12 years of age (with adult supervision): 2 or 3 sprays in each nostrill not more often than every 10 to 12 hours. Do not exceed 2 doses in any 24-hour period.
- children under 6 years of age: consult a doctor.

To spray, squeeze bottle quickly and firmly. Do not tilt head backward while spraying. Wipe nozzle clean after use.

STORAGE AND HANDLING

- store between 20°C to 25°C (68° to 77° F)
- retain carton for future reference on full labeling

Inactive Ingredients

benzalkonium chloride solution, edetate disodium, polyethylene glycol, povidone, propylene glycol, purified water, sodium phosphate monobasic, sodium phosphate dibasic

HOW SUPPLIED

(pack: 30ml) NDC# 73414-002-02

(pack: 15ml) NDC# 73414-002-13

Manufactured by:

Seaway Pharma Inc.

Massena, NY 13662